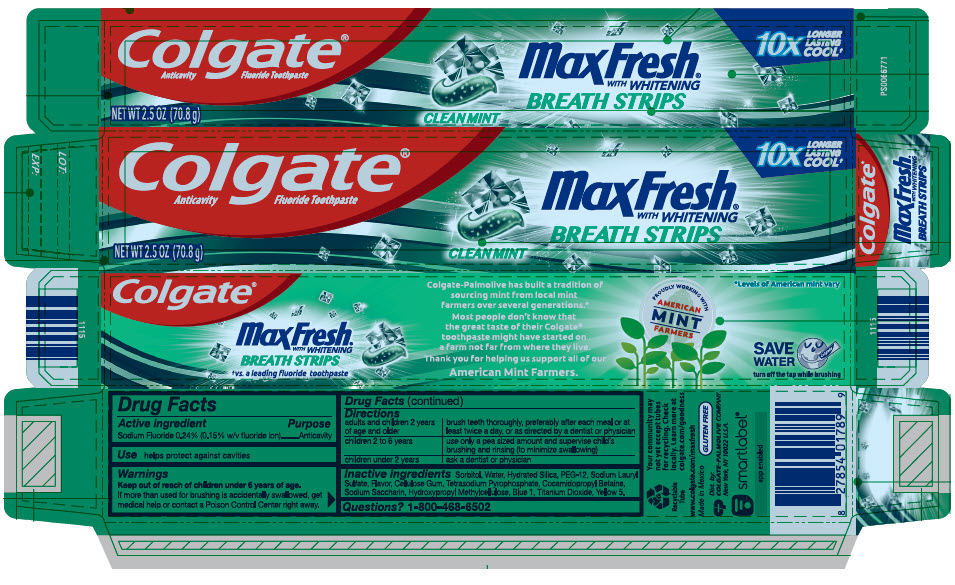 DRUG LABEL: Colgate
NDC: 35000-430 | Form: GEL, DENTIFRICE
Manufacturer: Colgate-Palmolive Company
Category: otc | Type: HUMAN OTC DRUG LABEL
Date: 20240617

ACTIVE INGREDIENTS: SODIUM FLUORIDE 1.1 mg/1 g
INACTIVE INGREDIENTS: SORBITOL 564.38 mg/1 g; WATER; HYDRATED SILICA; POLYETHYLENE GLYCOL 600; SODIUM LAURYL SULFATE; CARBOXYMETHYLCELLULOSE; GLYCERIN; COCAMIDOPROPYL BETAINE; SACCHARIN SODIUM; POWDERED CELLULOSE; FD&C BLUE NO. 1; TITANIUM DIOXIDE; FD&C YELLOW NO. 5

Colgate®
Max Fresh Clean Mint

Drug Facts

Active ingredient

Sodium Fluoride 0.24% (0.15% w/v fluoride ion)

Purpose

Anticavity

Use

helps protect against cavities

Warnings

Keep out of reach of children under 6 years of age.

If more than used for brushing is accidentally swallowed, get medical help or contact a Poison Control Center right away.

Directions

adults and children 2 years of age and older | brush teeth thoroughly, preferably after each meal or at least twice a day, or as directed by a dentist or physician
children 2 to 6 years | use only a pea sized amount and supervise child's brushing and rinsing (to minimize swallowing)
children under 2 years | ask a dentist or physician

Inactive ingredients

Sorbitol, Water, Hydrated Silica, PEG-12, Sodium Lauryl Sulfate, Flavor, Cellulose Gum, Tetrasodium Pyrophosphate, Cocamidopropyl Betaine, Sodium Saccharin, Hydroxypropyl Methylcellulose, Blue 1, Titanium Dioxide, Yellow 5.

Questions?

1-800-468-6502

Dist. by:
COLGATE-PALMOLIVE COMPANY
New York, NY 10022 U.S.A.

PRINCIPAL DISPLAY PANEL - 70.8 g Tube Carton

Colgate®
Anticavity
Fluoride Toothpaste

10x
LONGER
LASTING
COOL†

MaxFresh®
WITH WHITENING
BREATH STRIPS

CLEAN MINT

NET WT 2.5 OZ (70.8 g)